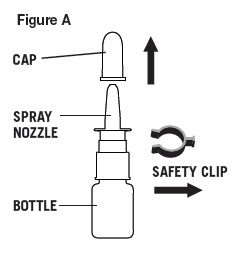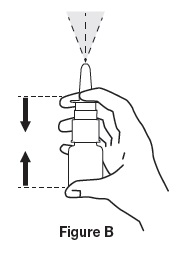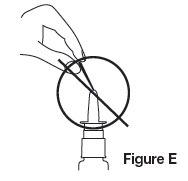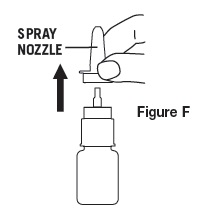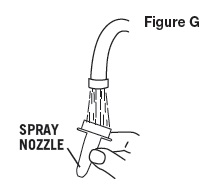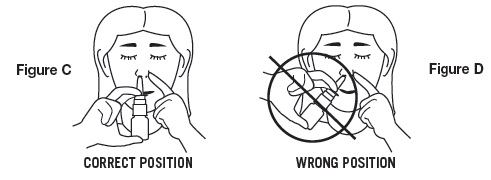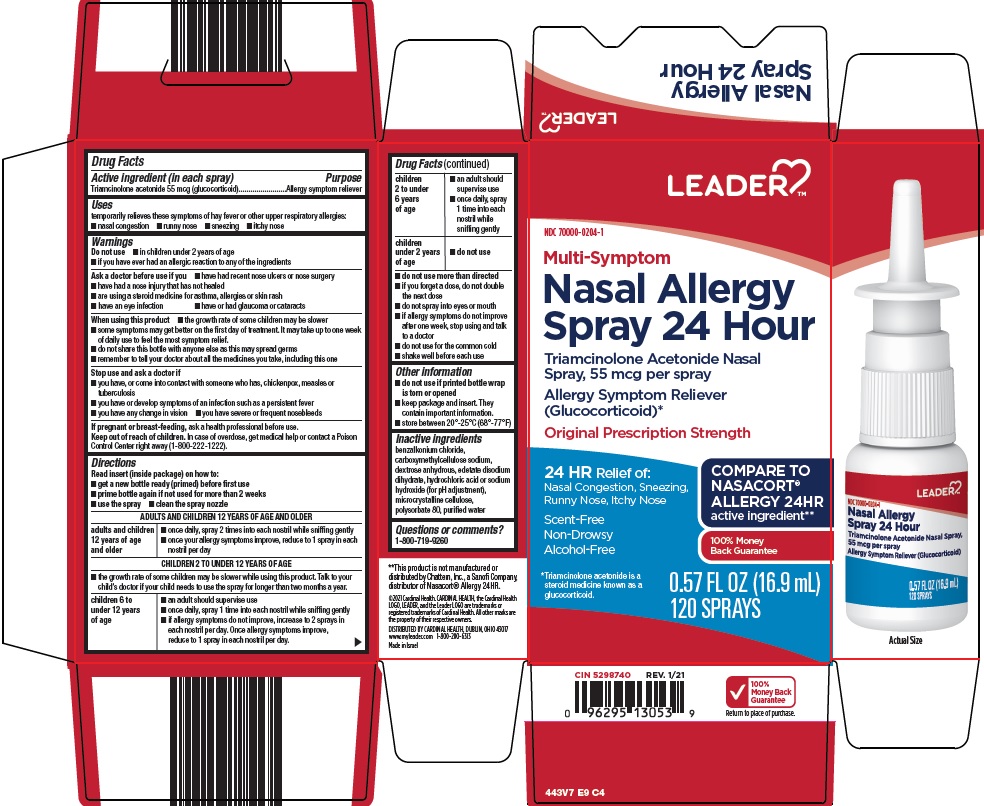 DRUG LABEL: Leader Nasal Allergy
NDC: 70000-0204 | Form: SPRAY, METERED
Manufacturer: Cardinal Health 110, LLC. dba Leader
Category: otc | Type: HUMAN OTC DRUG LABEL
Date: 20260225

ACTIVE INGREDIENTS: TRIAMCINOLONE ACETONIDE 55 ug/1 1
INACTIVE INGREDIENTS: BENZALKONIUM CHLORIDE; CARBOXYMETHYLCELLULOSE SODIUM, UNSPECIFIED; ANHYDROUS DEXTROSE; EDETATE DISODIUM; HYDROCHLORIC ACID; SODIUM HYDROXIDE; MICROCRYSTALLINE CELLULOSE; POLYSORBATE 80; WATER

Cardinal Health Nasal Allergy Spray 24 Hour Drug Facts

Active ingredient (in each spray)

Triamcinolone acetonide 55 mcg (glucocorticoid)

Purpose

Allergy symptom reliever

Uses

temporarily relieves these symptoms of hay fever or other upper respiratory allergies:

- nasal congestion
- runny nose
- sneezing
- itchy nose

Warnings

Do not use

- in children under 2 years of age
- if you have ever had an allergic reaction to any of the ingredients

Ask a doctor before use if

- have had recent nose ulcers or nose surgery
- have had a nose injury that has not healed
- are using a steroid medicine for asthma, allergies or skin rash
- have an eye infection
- have or had glaucoma or cataracts

When using this product

- the growth rate of some children may be slower
- some symptoms may get better on the first day of treatment. It may take up to one week of daily use to feel the most symptom relief.
- do not share this bottle with anyone else as this may spread germs
- remember to tell your doctor about all the medicines you take, including this one

Stop use and ask a doctor if

- you have, or come into contact with someone who has, chickenpox, measles or tuberculosis
- you have or develop symptoms of an infection such as a persistent fever
- you have any change in vision
- you have severe or frequent nosebleeds

If pregnant or breast-feeding,

ask a health professional before use.

Keep out of reach of children.

In case of overdose, get medical help or contact a Poison Control Center right away (1-800-222-1222).

Directions

Read insert (inside package) on how to:

- get a new bottle ready (primed) before first use
- prime bottle again if not used for more than 2 weeks
- use the spray
- clean the spray nozzle

ADULTS AND CHILDREN 12 YEARS OF AGE AND OLDER
adults and children 12 years of age and older | - once daily, spray 2 times into each nostril while sniffing gently - once your allergy symptoms improve, reduce to 1 spray in each nostril per day
CHILDREN 2 TO UNDER 12 YEARS OF AGE
- the growth rate of some children may be slower while using this product. Talk to your child’s doctor if your child needs to use the spray for longer than two months a year.
children 6 to under 12 years of age | - an adult should supervise use - once daily, spray 1 time into each nostril while sniffing gently - if allergy symptoms do not improve, increase to 2 sprays in each nostril per day. Once allergy symptoms improve, reduce to 1 spray in each nostril per day.
children 2 to under 6 years of age | - an adult should supervise use - once daily, spray 1 time into each nostril while sniffing gently
children under 2 years of age | - do not use

- do not use more than directed
- if you forget a dose, do not double the next dose
- do not spray into eyes or mouth
- if allergy symptoms do not improve after one week, stop using and talk to a doctor
- do not use for the common cold
- shake well before each use

Other information

- do not use if printed bottle wrap is torn or opened
- keep package and insert. They contain important information.
- store between 20o-25oC (68o-77oF)

Inactive ingredients

benzalkonium chloride, carboxymethylcellulose sodium, dextrose anhydrous, edetate disodium dihydrate, hydrochloric acid or sodium hydroxide (for pH adjustment), microcrystalline cellulose, polysorbate 80, purified water

Questions or comments?

1-800-719-9260

Consumer information

Triamcinolone Acetonide Nasal Spray 55 mcg per spray

IMPORTANT INFORMATION

- Read both sides of this insert for complete instructions on how to get a bottle ready (primed), how to use the spray bottle and how to clean the spray nozzle.
- Keep this insert as it contains important information.

STEPS TO GET A NEW BOTTLE READY FOR USE (PRIMED)

1. Before first use, a new bottle must be primed.

a. Remove cap and safety clip (Figure A).
b. Shake bottle.
c. Press and release spray nozzle until a fine mist is produced (as shown in Figure B). This may take several times. Take care not to spray in face.

PRIME BOTTLE AGAIN IF NOT USED FOR MORE THAN 2 WEEKS

- Repeat steps for priming a bottle (see above).

USE INSTRUCTIONS

1. Blow nose gently to clear nostrils.
2. Remove cap and safety clip, then shake bottle.
3. Hold bottle with thumb under bottle and spray nozzle between fingers (as shown in Figure B).
4. Press against the outside of your nose with your finger to close off one nostril (as shown in Figure C).
5. Place the tip of the spray nozzle into the other nostril. The spray nozzle should not reach far into the nose. Aim nozzle toward back of nose (as shown in Figure C).

DO NOT spray toward nasal septum (the wall between the 2 nostrils) (as shown in Figure D).

6. While sniffing gently, spray into nostril.

IMPORTANT: For complete dosing instructions, See “Directions for use” on next side.

7. Repeat steps “4” through “6” for the other nostril.
8. After using the nasal spray, wipe nozzle with a tissue, replace safety clip, and replace cap by pressing it down over the spray nozzle.

NOTE: Avoid blowing nose for 15 minutes after use.

If nozzle does not spray properly, see cleaning instructions on next side.

(continued on side 2)

SIDE 1

DIRECTIONS FOR USE

- BEFORE first use, you must get a new bottle ready (primed).
- If bottle is not used for more than 2 weeks, prime bottle again.

Dosing

ADULTS AND CHILDREN 12 YEARS OF AGE AND OLDER

adults and children 12 years of age and older

- once daily, spray 2 times into each nostril while sniffing gently
- once your allergy symptoms improve, reduce to 1 spray in each nostril per day

CHILDREN 2 TO UNDER 12 YEARS OF AGE

- the growth rate of some children may be slower while using this product. Talk to your child’s doctor if your child needs to use the spray for longer than two months a year.

children 6 to under 12 years of age

- an adult should supervise use
- once daily, spray 1 time into each nostril while sniffing gently
- if allergy symptoms do not improve, increase to 2 sprays in each nostril per day. Once allergy symptoms improve, reduce to 1 spray in each nostril per day.

children 2 to under 6 years of age

- an adult should supervise use
- once daily, spray 1 time into each nostril while sniffing gently

children under 2 years of age

- do not use

Other important information for use

- Do not use more than directed.
- If you forget a dose, do not double the next dose.
- Do not spray into eyes or mouth.
- If you get the spray in your eyes, rinse well with water.
- If allergy symptoms do not improve after one week, stop using and talk to a doctor.
- Do not share this bottle with anyone else as this may spread germs.

IF PUMP DOES NOT SPRAY PROPERLY, THE NOZZLE MAY BE BLOCKED

1. Never try to unblock nozzle with a pin or any other object (as shown in Figure E).
2. Clean the nozzle as shown below.

CLEANING INSTRUCTIONS

1. Gently pull spray nozzle away from bottle (as shown in Figure F).
2. Rinse SPRAY NOZZLE ONLY under warm water (as shown in Figure G).
3. Shake or tap to remove excess water.
4. Re-attach spray nozzle to bottle.
5. Press and release spray nozzle until a fine spray is produced, taking care not to spray in face.

Triamcinolone Acetonide Nasal Spray pump is now ready to use.

Where can I get more information? 1-800-719-9260

Store between 20°-25°C (68°-77°F)

Made in Israel

Distributed By

Perrigo®

Allegan, MI 49010

SIDE 2

: 44300 00 J4

Package/Label Principal Display Panel

LEADER TM

Multi-Symptom

Nasal Allergy Spray 24 Hour

Triamcinolone Acetonide Nasal Spray, 55 mcg per spray

Allergy Symptom Reliever (Glucocorticoid)*

Original Prescription Strength

24 HR Relief of: Nasal Congestion, Sneezing, Runny Nose, Itchy Nose

COMPARE TO NASACORT® ALLERGY 24HR active ingredient

Scent-Free

Non-Drowsy

Alcohol-Free

100% Money Back Guarantee

*Triamcinolone acetonide is a steroid medicine known as a glucocorticoid.

0.57 FL OZ (16.9 mL) 120 SPRAYS